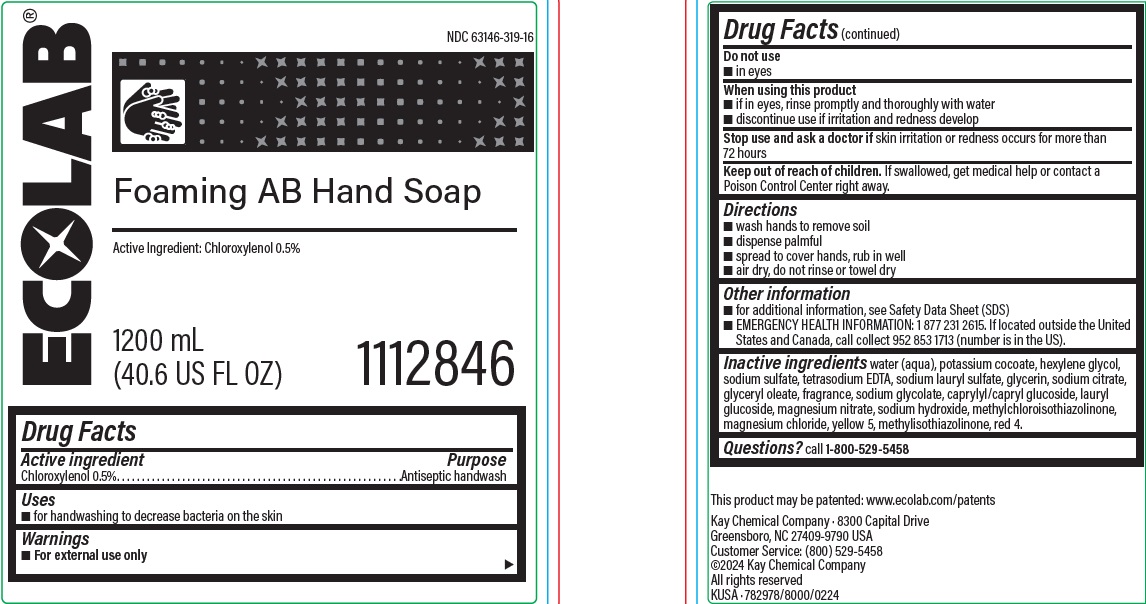 DRUG LABEL: FOAMING AB HANDSOAP
NDC: 47593-691 | Form: LIQUID
Manufacturer: Ecolab Inc.
Category: otc | Type: HUMAN OTC DRUG LABEL
Date: 20251230

ACTIVE INGREDIENTS: CHLOROXYLENOL 5 mg/1 mL
INACTIVE INGREDIENTS: WATER; POTASSIUM COCOATE; HEXYLENE GLYCOL; SODIUM SULFATE; EDETATE SODIUM; SODIUM LAURYL SULFATE; GLYCERIN; SODIUM CITRATE; GLYCERYL OLEATE; SODIUM GLYCOLATE; DECYL GLUCOSIDE; LAURYL GLUCOSIDE; MAGNESIUM NITRATE; SODIUM HYDROXIDE; METHYLCHLOROISOTHIAZOLINONE; MAGNESIUM CHLORIDE; FD&C YELLOW NO. 5; METHYLISOTHIAZOLINONE; FD&C RED NO. 4

Drug Facts

Active ingredient

Chloroxylenol 0.5%

Purpose

Antiseptic handwash

Uses

- For handwashing to decrease bacteria on the skin

Warnings

- For external use only

Do not use

- In eyes

When using this product

- If in eyes, rinse promptly and thoroughly with water
- Discontinue use if irritation and redness develop

Stop use and ask a doctor if

- skin irritation or redness occurs for more than 72 hours

Keep out of reach of children. If swallowed, get medical help or contact a Poison Control Center right away.

Directions

- wash hands to remove soil
- dispense palmful
- spread to cover hands, rub in well
- air dry, do not rinse or towel dry

Other information

- for additional infomration see Safety Data Sheet (SDS)
- EMERGENCY HEALTH INFORMATION: 1 877 231 2615. If located outside the United States and Canada, call collect 952 853 1713 (number is in the US).

INACTIVE INGREDIENT

Inactive ingredients water (aqua), potassium cocoate, hexylene glycol, sodium sulfate, tetrasodium edta, sodium lauryl sulfate, glycerin, sodium citrate, glyceryl oleate, fragrance, sodium glycolate, caprylyl/capryl glucoside, lauryl glucoside, magnesium nitrate, sodium hydroxide, methylchloroisothiazolinone, magnesium chloride, yellow 5, methylisothiazolinone, red 4

Questions? call 1-800-529-5458

Principal display panel and representative label

ECOLAB

Foaming AB Hand Soap

Active Ingredient: Chloroxylenol 0.5%

1200 mL

(40.6 US FL OZ) 1112846

Kay Chemical Company · 8300 Capital Drive

Greensboro, NC 27409-9790 USA

Customer Service: (800) 529-5458

©2024 Kay Chemical Company

All rights reserved

KUSA · 782978/8000/0224